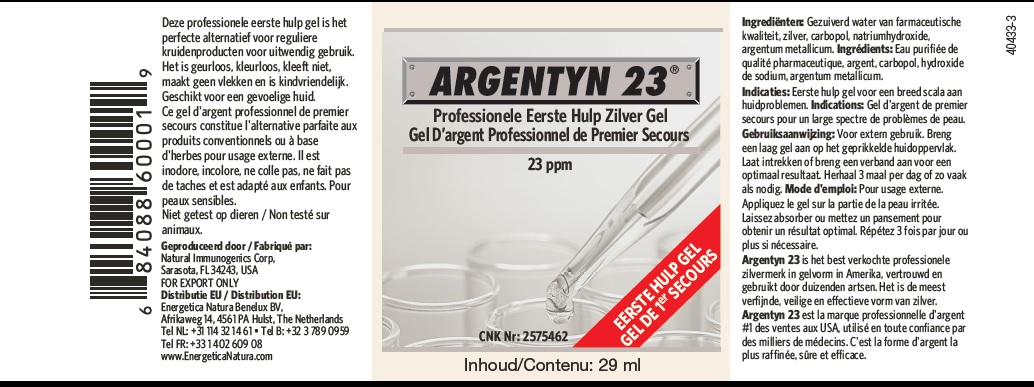 DRUG LABEL: Argentyn 23Professionele Eer




NDC: 52166-009 | Form: GEL
Manufacturer: Natural Immunogenics Corp.dba SOVEREIGN NATURALS
Category: otc | Type: HUMAN OTC DRUG LABEL
Date: 20250522

ACTIVE INGREDIENTS: SILVER 23 mg/1000 mL
INACTIVE INGREDIENTS: WATER; CARBOMER HOMOPOLYMER TYPE B (ALLYL PENTAERYTHRITOL CROSSLINKED); SODIUM HYDROXIDE

DRUG FACTS

ACTIVE INGREDIENT

Ingredienten: zilver [argentum metallicum]

Ingredients: argent [argentum metallicum]

INACTIVE INGREDIENT

Ingredienten: Gezuiverd water van farmaceutische

kwaliteit, carbopol, natriumhydroxide.

Ingredients: Eau ourifiee de qualite

pharmaceutique, carbopol, hydroxide

de sodium

PURPOSE

Deze professionele eerste hulp gel is het
perfecte alternatief voor reguliere
kruidenproducten voor uitwendig gebruik.
Het is geurloos, kleurloos, kleeft niet,
maakt geen vlekken en is kindvriendelijk.
Geschikt voor een gevoelige huid.
Ce gel d'argent professionnel de premier
secours constitue l'alternative parfaite aux
produits conventionnels ou à base
d'herbes pour usage externe. Il est
inodore, incolore, ne colle pas, ne fait pas
de taches et est adapté aux enfants. Pour
peaux sensibles.

DESCRIPTION

Niet getest op dieren / Non teste sur animaux

INDICATIONS AND USAGE

Indicaties: Antomicrobiele gel voor een breed scala

aan huidproblemen.

Indications: Gel antomicrobien

pour un large spectre de problemes de peau.

DOSAGE AND ADMINISTRATION

Gebruiksaanwijzing: Voor extern gebruik. Breng

een laaggel aan op de aangedane huidoppervlakte.

Laat intrekken of breng een verband aan voor een

optimal resultaat. Herhaal 3 maal per dag of zo vaak

als nodig.

Mode d'emploi: pour usage externe.

Appliquez le gel sur la partie de la peau concernee.

Laissez absorber ou ettez un pasnsement pour

pbtenir un resultat optimal. Repetez 3 fois par jour ou

plus si necessaire.

DESCRIPTION

Argentyn 23 is het best verkochte professionele

zilvermerk in gelvorm in Amerika, vertrouwd en

gebruikt door duizenden artsen. Het is de meest verfijnde, veilige en effectieve

vorm van zilver.

Argentyn 23 est la marque professionelle d'argent

No. 1 des ventes aux USA, utilise en toute confiance par

des millars de medicins. C'est la forme d'argent

la plus raffinee, sure et efficace.